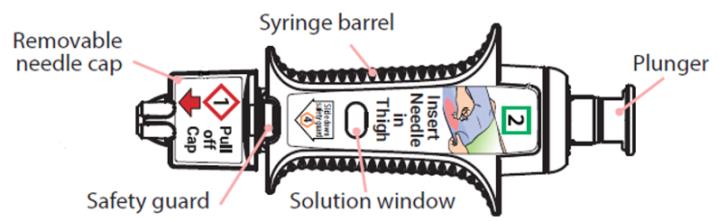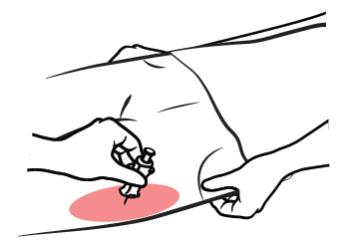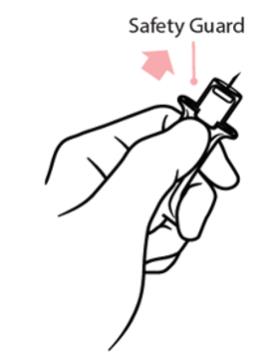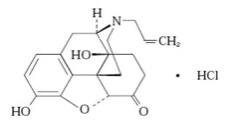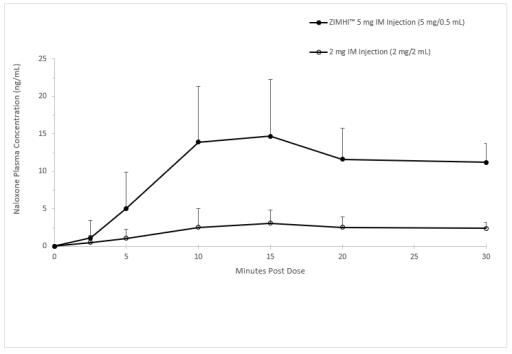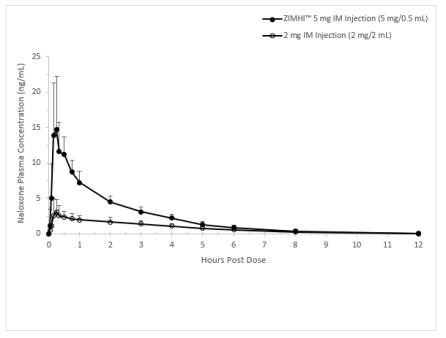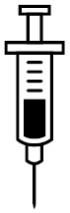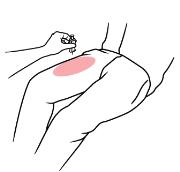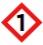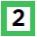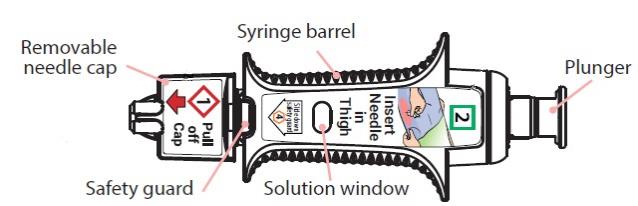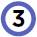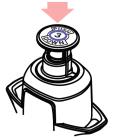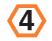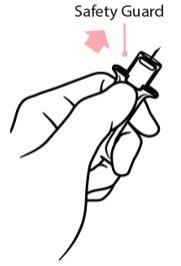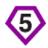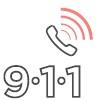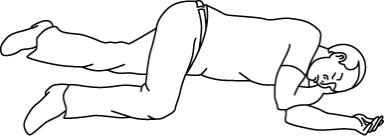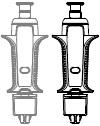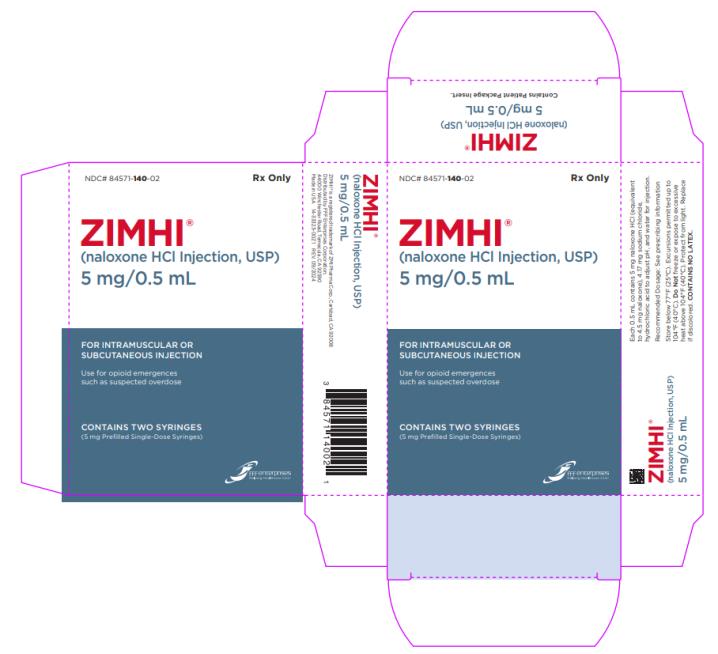 DRUG LABEL: ZIMHI
NDC: 84571-140 | Form: INJECTION, SOLUTION
Manufacturer: ZMI Pharma Inc.
Category: prescription | Type: HUMAN PRESCRIPTION DRUG LABEL
Date: 20251204

ACTIVE INGREDIENTS: NALOXONE HYDROCHLORIDE 5 mg/0.5 mL
INACTIVE INGREDIENTS: SODIUM CHLORIDE 4.17 mg/0.5 mL; HYDROCHLORIC ACID; WATER

HIGHLIGHTS OF PRESCRIBING INFORMATION

ZIMHI ® (naloxone hydrochloride injection, USP)
These highlights do not include all the information needed to use ZIMHI ® safely and effectively. See full prescribing information for ZIMHI®.
ZIMHI® (naloxone hydrochloride injection, USP) prefilled syringefor intramuscular or subcutaneous use 5 mg/0.5 mL.
Initial U.S. Approval: 1971

1. INDICATIONS AND USAGE

ZIMHI is an opioid antagonist indicated for the emergency treatment of known or suspected opioid overdose, as manifested by respiratory and/or central nervous system depression. (1)

ZIMHI is intended for immediate administration as emergency therapy in settings where opioids may be present. (1)

ZIMHI is not a substitute for emergency medical care. (1)

2. DOSAGE AND ADMINISTRATION

- ZIMHI is for intramuscular or subcutaneous use only. (2.1)
- Seek emergency medical care immediately after use. (2.1)
- ZIMHI is intended to be administered by individuals 12 years of age or older. (2.1)
- Administer ZIMHI to adult or pediatric patients into the anterolateral aspect of the thigh, through clothing if necessary. (1)
- See the Full Prescribing Information and Instructions for Use for important information on how to safely administer ZIMHI. (2.1)
- Keep the patient under continued surveillance until emergency personnel arrive and administer repeated doses of ZIMHI as necessary. (2.1)
- Additional supportive and/or resuscitative measures may be helpful while awaiting emergency medical assistance. (2.2)
- In pediatric patients under the age of one, the caregiver should pinch the thigh muscle while administering the dose. (2.2)

3. DOSAGE FORMS AND STRENGTHS

Injection: 5 mg/0.5 mL naloxone hydrochloride solution in a pre-filled prefilled syringe. (3)

4. CONTRAINDICATIONS

Hypersensitivity to naloxone hydrochloride or to any of the other ingredients in ZIMHI. (4)

5. WARNINGS AND PRECAUTIONS

- Risk of Recurrent Respiratory and CNS Depression: Due to the duration of action of naloxone relative to the opioid, respiratory and CNS depression may recur after the first dose of naloxone. Seek emergency medical assistance immediately after the first dose, keep the patient under continued surveillance, and administer repeated doses of naloxone using a new ZIMHI, as necessary, while awaiting emergency medical assistance. (5.1)
- Risk of Limited Efficacy with Partial Agonists or Mixed Agonists/Antagonists: Reversal of respiratory depression caused by partial agonists or mixed agonists/antagonists such as buprenorphine and pentazocine, may be incomplete. Larger or repeat doses may be required. (5.2)
- Precipitation of Severe Opioid Withdrawal: Use in patients who are opioid dependent results in rapid onset of opioid withdrawal. In neonates, opioid withdrawal may be life-threatening if not recognized and properly treated. Monitor for the development of opioid withdrawal. (5.3)
- Risk of Cardiovascular (CV) Effects: Abrupt postoperative reversal of opioid depression may result in adverse CV effects. These events have primarily occurred in patients who had pre-existing CV disorders or received other drugs that may have similar CV effects. Monitor these patients closely in an appropriate healthcare setting after use of naloxone hydrochloride. (5.3)
- Risk of Accidental Needlestick Injury: After use, the ZIMHI needle is exposed until the safety guard is deployed. Stress to patients the importance of familiarizing themselves with the device and its operation prior to experiencing an emergency situation, and to immediately seek medical attention should a needlestick occur. (5.4)

6. ADVERSE REACTIONS

The following adverse reactions were most commonly observed in ZIMHI clinical studies: dizziness and injection site erythema. (6)

To report SUSPECTED ADVERSE REACTIONS, contact ZMI Pharma Corporation at 1-800-230-3935 or FDA at 1-800-FDA-1088 or www.fda.gov/medwatch.

FULL PRESCRIBING INFORMATION

1. INDICATIONS AND USAGE

ZIMHI is indicated in adults and pediatric patients for:

- the emergency treatment of known or suspected opioid overdose, as manifested by respiratory and/or central nervous system depression.

ZIMHI is intended for immediate administration as emergency therapy in settings where opioids may be present.

ZIMHI is not a substitute for emergency medical care.

2. DOSAGE AND ADMINISTRATION

2.1 Important Administration Instructions

ZIMHI is for intramuscular and subcutaneous use only.

Because treatment of known or suspected opioid overdose must be performed by someone other than the patient, instruct the prescription recipient to inform those around them about the presence of ZIMHI and the Instructions for Use.

ZIMHI is intended to be administered by individuals 12 years of age or older.Younger individuals or those with limited hand strength may find the device difficult to use.

ZIMHI is light sensitive. Store ZIMHI in the outer case provided to protect it from light.

Prior to a medical emergency (during storage), periodically visually inspect ZIMHI through the viewing window on the device. If the solution is discolored yellow or brown color, cloudy, or contains particles, replace ZIMHI with a new one [ see How Supplied/Storage and Handling (16.2)].

Do not attempt to reuse ZIMHI. Each ZIMHI contains a single-dose of naloxone hydrochloride for single-dose injection.

Instruct the patient or caregiver to read the Instructions for Use at the time they receive a prescription for ZIMHI®. Emphasize the following instructions to the patient or caregiver:

- Seek emergency medical care immediately after use. Because the duration of action of most opioids exceeds that of naloxone hydrochloride and the suspected opioid overdose may occur outside of supervised medical settings, seek immediate emergency medical assistance, keep the patient under continued surveillance until emergency personnel arrive, and administer repeated doses of ZIMHI as necessary. Always seek emergency medical assistance in the event of a suspected potentially life-threatening opioid emergency after administration of the first dose of ZIMHI.
- Additional doses of ZIMHI may be required until emergency medical assistance becomes available [ see Dosage and Administration (2.2)].
- Administer ZIMHI according to the Instructions for Use and the printed instructions on the device label:
  - Place the patient in the supine position.
  - Inject ZIMHI intramuscularly or subcutaneously into the anterolateral aspect of the thigh with the needle facing downwards. Inject through clothing if necessary [ see Instructions for Use].
  - Embed the needle completely before transferring the thumb to the syringe plunger.

- Immediately after injection, using one hand with fingers behind the needle, slide the safety guard over the needle. Do not use two hands to activate the safety guard.

- Never put thumb, fingers, or hand over the exposed needle. Failure to follow these instructions may result in a needlestick injury. If an accidental needlestick occurs, get medical help immediately [ see Warnings and Precautions (5.4)].
- Do NOT attempt to re-cap the needle with the needle cap once it has been removed [ see Warnings and Precautions (5.4)].
- Place the patient in the lateral recumbent position (recovery position).
- ZIMHI must be used and/or properly disposed of as described below once the protective cap covering the needle is removed.
- Put the used syringe into the blue case, close the case, and give your used ZIMHI syringe to the healthcare provider for inspection and proper disposal.
- Tell the healthcare provider that you have received or administered an injection of naloxone HCl. Show the healthcare provider where the injection was administered.

2.2 Dosing Information

Initial Dosing

Administer the initial dose of ZIMHI®to adult or pediatric patients intramuscularly or subcutaneously into the anterolateral aspect of the thigh, through clothing if necessary, and seek emergency medical assistance. Administer ZIMHI®as quickly as possible because prolonged respiratory depression may result in damage to the central nervous system or death.

Repeat Dosing

The requirement for repeat doses of ZIMHI depends upon the amount, type, and route of administration of the opioid being antagonized.

If the desired response is not obtained after 2 or 3 minutes, an additional dose of ZIMHI may be administered. If there is still no response and additional doses are available, additional doses of ZIMHI may be administered every 2 to 3 minutes until emergency medical assistance arrives.

Additional supportive and/or resuscitative measures may be helpful while awaiting emergency medical assistance.

If the patient responds to ZIMHI and relapses back into respiratory depression before emergency assistance arrives, administer an additional dose of ZIMHI and continue surveillance of the patient after administering an additional dose.

Reversal of respiratory depression by partial agonists or mixed agonist/antagonists, such as buprenorphine and pentazocine, may be incomplete and may require higher doses of naloxone hydrochloride or repeated administration of ZIMHI.

Dosing in Adults and Pediatric Patients

Instruct patients or their caregivers to administer ZIMHI according to the Instructions for Use, intramuscularly or subcutaneously.

Dosing in Pediatric Patients under Age One Year

In pediatric patients under the age of one year, the caregiver should pinch the thigh muscle while administering ZIMHI. Carefully observe the administration site for signs of infection following resolution of the opioid emergency.

3. DOSAGE FORMS AND STRENGTHS

Injection: 5 mg/0.5 mL naloxone hydrochloride is a clear, colorless to slightly yellow, sterile solution in a single-dose, pre-filled syringe. Each ZIMHI 5 mg delivers 5 mg naloxone hydrochloride (equivalent to 4.5 mg naloxone) injection, USP (0.5 mL).

4. CONTRAINDICATIONS

ZIMHI is contraindicated in patients known to be hypersensitive to naloxone hydrochloride or to any of the other ingredients.

5. WARNINGS AND PRECAUTIONS

5.1 Risk of Recurrent Respiratory and Central Nervous System Depression

The duration of action of most opioids may exceed that of ZIMHI resulting in a return of respiratory and/or central nervous system depression after an initial improvement in symptoms. Therefore, it is necessary to seek emergency medical assistance immediately after delivering the first dose of ZIMHI. Keep the patient under continued surveillance and administer additional doses of ZIMHI if the patient is not adequately responding or responds and then relapses back into respiratory depression, as necessary [ see Dosage and Administration (2.2)]. Additional supportive and/or resuscitative measures may be helpful while awaiting emergency medical assistance.

5.2 Risk of Limited Efficacy with Partial Agonists or Mixed Agonist/Antagonists

Reversal of respiratory depression by partial agonists or mixed agonist/antagonists such as buprenorphine and pentazocine, may be incomplete. Larger or repeat doses of naloxone hydrochloride may be required to antagonize buprenorphine because the latter has a long duration of action due to its slow rate of binding and subsequent slow dissociation from the opioid receptor [ see Dosage and Administration (2)]. Buprenorphine antagonism is characterized by a gradual onset of the reversal effects and a decreased duration of action of the normally prolonged respiratory depression.

5.3 Precipitation of Severe Opioid Withdrawal

The use of ZIMHI in patients who are opioid dependent results in opioid withdrawal characterized by rapid onset of severe body aches, vomiting, diarrhea, tachycardia, fever, runny nose, sneezing, piloerection, sweating, yawning, nausea, nervousness, restlessness or irritability, shivering or trembling, abdominal cramps, weakness, and increased blood pressure. In neonates, opioid withdrawal may be life-threatening if not recognized and properly treated and may include the following signs and symptoms: convulsions, excessive crying, and hyperactive reflexes. Monitor patients for the development of the signs and symptoms of opioid withdrawal.

Abrupt postoperative reversal of opioid depression after using naloxone hydrochloride may result in nausea, vomiting, sweating, tremulousness, tachycardia, hypotension, hypertension, seizures, ventricular tachycardia and fibrillation, pulmonary edema, and cardiac arrest. Death, coma, and encephalopathy have been reported as sequelae of these events. These events have primarily occurred in patients who had pre-existing cardiovascular disorders or received other drugs that may have similar adverse cardiovascular effects. Although a direct cause and effect relationship has not been established, after use of naloxone hydrochloride, monitor patients with pre-existing cardiac disease or patients who have received medications with potential adverse cardiovascular effects for hypotension, ventricular tachycardia or fibrillation, and pulmonary edema in an appropriate healthcare setting. It has been suggested that the pathogenesis of pulmonary edema associated with the use of naloxone hydrochloride is similar to neurogenic pulmonary edema, i.e., a centrally mediated massive catecholamine response leading to a dramatic shift of blood volume into the pulmonary vascular bed resulting in increased hydrostatic pressures.

There may be clinical settings, particularly the postpartum period in neonates with known or suspected exposure to maternal opioid use, where it is preferable to avoid the abrupt precipitation of opioid withdrawal symptoms. In these settings, consider use of an alternative naloxone product which can be titrated to effect and, where applicable, dosed according to weight [ see Use in Specific Populations (8.4)].

5.4 Risk of Accidental Needlestick Injury

After use, the ZIMHI needle is exposed until the safety guard is deployed. A needlestick injury could occur during use in emergency situations. In the event that an accidental needlestick occurs, medical attention should be sought. Potential exposure to blood borne pathogens including HIV, HBV, and HCV requires immediate evaluation by a medical professional. Stress to patients the importance of familiarizing themselves with the device and its operation prior to experiencing an emergency situation, so they are familiar with the safety guard and its deployment.

6. ADVERSE REACTIONS

The following serious adverse reactions are discussed elsewhere in the labeling:

- Precipitation of Severe Opioid Withdrawal [ see Warnings and Precautions (5.3)]

Because clinical studies are conducted under widely varying conditions, adverse reaction rates observed in the clinical studies of a drug cannot be directly compared to the rates in the clinical studies of another drug and may not reflect the rates observed in practice.

The following adverse reactions were observed in ZIMHI clinical studies in healthy volunteers without opioid dependence: nausea, dizziness, lightheadedness, and elevated bilirubin.

The following adverse reactions have been identified during post-approval use of naloxone hydrochloride in the post-operative setting. Because these reactions are reported voluntarily from a population of uncertain size, it is not always possible to reliably estimate their frequency or establish a causal relationship to drug exposure: Hypotension, hypertension, ventricular tachycardia and fibrillation, dyspnea, pulmonary edema, and cardiac arrest. Death, coma, and encephalopathy have been reported as sequelae of these events. Excessive doses of naloxone hydrochloride in post-operative patients have resulted in significant reversal of analgesia and have caused agitation [ see Warnings and Precautions (5.3)].

Other events that have been reported in post-marketing use of naloxone hydrochloride include agitation, disorientation, confusion, and anger.

Abrupt reversal of opioid effects in persons who were opioid dependent resulted in opioid withdrawal characterized by rapid onset of severe body aches, vomiting, diarrhea, tachycardia, fever, runny nose, sneezing, piloerection, sweating, yawning, nausea, nervousness, restlessness or irritability, shivering or trembling, abdominal cramps, weakness, and increased blood pressure. In some patients, aggressive behavior has occurred in the context of abrupt reversal of an opioid overdose. In the neonate, opioid withdrawal signs and symptoms also included: convulsions, excessive crying, and hyperactive reflexes [ see Warnings and Precautions (5.3)].

8. USE IN SPECIFIC POPULATIONS

8.1 Pregnancy

Risk Summary

Life-sustaining therapy for opioid overdose should not be withheld (see Clinical Considerations). Available data from retrospective cohort studies on naloxone use in pregnant women have not identified a drug-associated risk of major birth defects or miscarriage. In animal reproduction studies, no embryotoxic or teratogenic effects were observed in mice and rats treated with naloxone hydrochloride during the period of organogenesis at doses equivalent to 4-times and 8-times, respectively, a human dose of 10 mg/day.

The estimated background risk of major birth defects and miscarriage for the indicated population is unknown. All pregnancies have a background risk of birth defect, loss, or other adverse outcomes. In the U.S. general population, the estimated background risk of major birth defects and miscarriage in clinically recognized pregnancies is 2% to 4% and 15% to 20%, respectively.

Clinical Considerations

Disease-associated maternal and/or embryo/fetal risk

An opioid overdose is a medical emergency and can be fatal for the pregnant woman and fetus if left untreated. Treatment with ZIMHI for opioid overdose should not be withheld because of potential concerns regarding the effects of ZIMHI on the fetus.

Data

Animal Data

Naloxone hydrochloride was administered during organogenesis to mice and rats at doses 4-times and 8-times, respectively, the dose of 10 mg/day given to a 50 kg human (when based on body surface area or mg/m^2). These studies demonstrated no embryotoxic or teratogenic effects due to naloxone hydrochloride.

8.2 Lactation

Risk Summary

Naloxone is minimally orally available and is unlikely to affect the breastfed infant. There is no information regarding the presence of naloxone in human milk, the effects of naloxone on the breastfed infant, or on milk production. Studies in nursing mothers have shown that naloxone does not affect prolactin or oxytocin hormone levels.

8.4 Pediatric Use

The safety and effectiveness of ZIMHI®(for intramuscular and subcutaneous use) have been established in pediatric patients of all ages for the emergency treatment of known or suspected opioid overdose as manifested by respiratory and/or central nervous system depression. Use of naloxone hydrochloride in all pediatric patients is supported by adult bioequivalence studies coupled with evidence from the safe and effective use of another naloxone hydrochloride injectable product. No pediatric studies were conducted for ZIMHI.

Absorption of naloxone hydrochloride following subcutaneous or intramuscular administration in pediatric patients may be erratic or delayed. Even when the opiate-intoxicated pediatric patient responds appropriately to naloxone hydrochloride injection, he/she must be carefully monitored for at least 24 hours as a relapse may occur as naloxone is metabolized.

In opioid-dependent pediatric patients, (including neonates), administration of naloxone hydrochloride may result in an abrupt and complete reversal of opioid effects, precipitating an acute opioid withdrawal syndrome. There may be clinical settings, particularly the postpartum period in neonates with known or suspected exposure to maternal opioid use, where it is preferable to avoid the abrupt precipitation of opioid withdrawal symptoms. Unlike acute opioid withdrawal in adults, acute opioid withdrawal in neonates manifesting as seizures may be life-threatening if not recognized and properly treated. Other signs and symptoms in neonates may include excessive crying and hyperactive reflexes. In these settings where it may be preferable to avoid the abrupt precipitation of acute opioid withdrawal symptoms, consider use of an alternative, naloxone hydrochloride product that can be dosed according to weight and titrated to effect. [ see Warnings and Precautions (5.3)].

In pediatric patients under the age of one year, the caregiver should pinch the thigh muscle while administering ZIMHI. Carefully observe the administration site for evidence of residual needle parts, signs of infection, or both. [ see Dosing Information (2.2)].

8.5 Geriatric Use

Geriatric patients have a greater frequency of decreased hepatic, renal, or cardiac function and of concomitant disease or other drug therapy. Therefore, the systemic exposure of naloxone can be higher in these patients.

Clinical studies of naloxone hydrochloride did not include sufficient numbers of subjects aged 65 and over to determine whether they respond differently from younger subjects. Other reported clinical experience has not identified differences in responses between the elderly and younger patients.

11. DESCRIPTION

ZIMHI (naloxone hydrochloride injection, USP) is an opioid antagonist supplied in a single-dose pre-filled syringe. ZIMHI is not made with natural rubber latex. Chemically, naloxone hydrochloride is the hydrochloride salt of 17-Allyl-4,5α-epoxy-3,14-dihydroxymorphinan-6-one hydrochloride with the following structure:

C19H21NO4• HCl

399.9 g/mol

Naloxone hydrochloride occurs as a white to slightly off-white powder, and is soluble in water, in dilute acids, and in strong alkali; slightly soluble in alcohol; practically insoluble in ether and in chloroform.

Each 0.5 mL contains 5 mg naloxone hydrochloride (equivalent to 4.5 mg naloxone), 4.17 mg sodium chloride, hydrochloric acid to adjust pH, and water for injection.

12. CLINICAL PHARMACOLOGY

12.1 Mechanism of Action

Naloxone hydrochloride is an opioid antagonist that antagonizes opioid effects by competing for the same receptor sites.

Naloxone hydrochloride reverses the effects of opioids, including respiratory depression, sedation, and hypotension. Also, it can reverse the psychotomimetic and dysphoric effects of agonist-antagonists such as pentazocine.

12.2 Pharmacodynamics

When naloxone hydrochloride is administered intravenously, the onset of action is generally apparent within two minutes. The time to onset of action is shorter for intravenous compared to subcutaneous or intramuscular routes of administration.

The duration of action is dependent upon the dose and route of administration of naloxone hydrochloride.

12.3 Pharmacokinetics

In a pharmacokinetic study of 14 healthy adults, a single intramuscular injection of 5 mg ZIMHI in a single-dose pre-filled syringe in a delivery device provides significantly higher Cmaxand AUC compared to a single intramuscular injection of 2 mg naloxone hydrochloride (1mg /1mL). Naloxone plasma concentration versus time profiles are shown in Figure 1.

The pharmacokinetic parameters of naloxone in plasma are shown in Table 1.

Table 1: Mean Pharmacokinetic Parameters (CV%) for Naloxone Following a Single Intramuscular Injection of 5 mg ZIMHI® (naloxone HCl) anda Single Intramuscular Injection of 2 mg Naloxone HCl in Healthy Subjects

Parameter | Intramuscular Injection of 5 mg ZIMHI (N = 14) | Intramuscular Injection of 2 mg Naloxone HCl (N = 14)
Tmax(h)* | 0.25 (0.17, 0.52) | 0.25 (0.05, 3.00)
Cmax(ng/mL) | 17.2 (44) | 3.58 (58.1)
AUC0-t(ng.h/mL) | 26.2 (21.5) | 9.43 (23.8)
AUC0-inf(ng.h/mL) | 26.6 (21.2) | 9.97 (22.6)
AUC0-0.04h(ng.h/mL) | 0.02 (208) | 0.01 (164)
AUC0-0.08h(ng.h/mL) | 0.15 (117) | 0.04 (128)
T1/2(h) | 1.50 (15.2) | 1.86 (28.9)

*tmaxreported as median (minimum, maximum)

Figure 1 Mean ± SD Plasma Concentration of Naloxone, (a) 0-30 minand (b) 0-12 h Following a Single Intramuscular Administration of 5 mg ZIMHIand a Single Intramuscular Administration of 2 mg Naloxone HCl

a)

b)

Distribution
Following parenteral administration, naloxone is distributed in the body and readily crosses the placenta. Plasma protein binding occurs but is relatively weak. Plasma albumin is the major binding constituent, but significant binding of naloxone also occurs to plasma constituents other than albumin. It is not known whether naloxone is excreted into human milk.

Elimination
Following a single 5 mg/0.5 mL mg ZIMHI injection, the mean plasma half-life of naloxone in healthy adults was 1.50 hours with values for individual subjects ranging from 1.18 to 1.87 hours. In a neonatal study of naloxone injection, the mean (± SD) plasma half-life was observed to be 3.1 (± 0.5) hours.

Metabolism
Naloxone hydrochloride is metabolized in the liver, primarily by glucuronide conjugation with naloxone-3-glucoronide as the major metabolite.

Excretion
After an oral or intravenous dose, about 25-40% of naloxone is excreted as metabolites in urine within 6 hours, about 50% in 24 hours, and 60-70% in 72 hours.

13. NONCLINICAL TOXICOLOGY

13.1 Carcinogenesis, Mutagenesis, Impairment of Fertility

Carcinogenesis

Long-term animal studies to evaluate the carcinogenic potential of naloxone have not been completed.

Mutagenesis

Naloxone was weakly positive in the Ames mutagenicity and in the in vitro human lymphocyte chromosome aberration test but was negative in the in vitro Chinese hamster V79 cell HGPRT mutagenicity assay and in the in vivo rat bone marrow chromosome aberration study.

Impairment of Fertility

Reproduction studies conducted in mice and rats at doses 4-times and 8-times, respectively, the dose of 10 mg/day given to a 50 kg human (when based on surface area or mg/m^2), demonstrated no adverse effect of naloxone hydrochloride on fertility.

16. HOW SUPPLIED/STORAGE AND HANDLING

16.1 How Supplied

ZIMHI (naloxone hydrochloride injection, USP) 5 mg/0.5 mL is a clear, colorless to slightly yellow, sterile solution provided as follows:

NDC 84571-140-11:Carton containing one case which contains one 5 mg/0.5 mL single-dose, pre-filled syringe

NDC 84571-140-02: Carton containing two cases, each of which contain one 5 mg/0.5 mL single-dose, pre-filled syringe per case

NDC 84571-140-11: Case containing one 5 mg/0.5 mL single-dose, pre-filled syringe

16.2 Storage and Handling

Store ZIMHI in the outer case provided.

Store below 77oF (25oC). Excursions permitted up to 104oF (40oC). Do Notfreeze or expose to excessive heat above 104oF (40oC). Protect from light.

Prior to a medical emergency (during storage), periodically visually inspect ZIMHI through the viewing window on the device. If the solution is discolored yellow or brown color, cloudy, or contains particles, replace ZIMHI with a new one.

17. PATIENT COUNSELING INFORMATION

Advise the patient and family members or caregivers to read the FDA-approved patient labeling (Patient Informationand Instructions for Use).

Instruct patients and their family members or caregivers to become familiar with all information contained in the case and carton as soon as they receive ZIMHI.

Inform patients of the following:

- ZIMHI is for the emergency treatment of known or suspected overdose.
- It is administered by a caregiver according to the Instructions for Use.
- After administration, the caregiver should get emergency help immediately.

Recognition of Opioid Overdose

Instruct the patients and their family members or caregivers how to recognize the signs and symptoms of an opioid overdose requiring the use of ZIMHI®such as the following:

- Extreme somnolence - inability to awaken a patient verbally or upon a firm sternal rub.
- Respiratory depression - this can range from slow or shallow respiration to no respiration in a patient who is unarousable.
- Other signs and symptoms that may accompany somnolence and respiratory depression include the following:
  - Miosis.
  - Bradycardia and/or hypotension.

Risk of Recurrent Respiratory and Central Nervous System Depression

Instruct patients and their family members or caregivers that, because the duration of action of most opioids may exceed that of ZIMHI, they must seek immediate emergency medical assistance after the first dose of ZIMHI and keep the patient under continued surveillance [ see Dosage and Administration (2.2), Warnings and Precautions (5.3)].

Limited Efficacy for/with Partial Agonists or Mixed Agonist/Antagonists

Instruct patients and their family members or caregivers that the reversal of respiratory depression caused by partial agonists or mixed agonist/antagonists such as buprenorphine and pentazocine, may be incomplete and may require higher doses of naloxone hydrochloride or repeated administration of ZIMHI [ see Dosage and Administration (2.2), Warnings and Precautions (5.3)].

Precipitation of Severe Opioid Withdrawal

Instruct patients and their family members or caregivers that the use of ZIMHI in patients who are opioid dependent may precipitate an acute abstinence syndrome characterized by the following signs and symptoms: body aches, diarrhea, tachycardia, fever, runny nose, sneezing, piloerection, sweating, yawning, nausea or vomiting, nervousness, restlessness or irritability, shivering or trembling, abdominal cramps, weakness, and increased blood pressure. In neonates, opioid withdrawal may be life threatening if not recognized and properly treated and may include the following signs and symptoms: convulsions, excessive crying, and hyperactive reflexes [ see Warnings and Precautions (5.3), Adverse Reactions (6)].

Administration Instructions

Instruct patients and their family members or caregivers to carefully read the Instructions for Use before an emergency arises. Emphasize the following important information:

- ZIMHI is intended to be administered by individuals 12 years of age or older.Younger individuals or those with limited hand strength may find the device difficult to use.
- Each syringe is for a single-dose injection.
- Make sure ZIMHI is present whenever persons may be intentionally or accidentally exposed to an opioid to treat serious opioid overdose (i.e., opioid emergencies).
- Administer ZIMHI as quickly as possible if a patient is unresponsive and an opioid overdose is suspected, even when in doubt, because prolonged respiratory depression may result in damage to the central nervous system or death. ZIMHI is not a substitute for emergency medical care [ see Dosage and Administration (2.1)].
- When removing the needle cap, there may be a drop of liquid on the needle: this is normal. The device contains an excess of liquid to ensure the required dose is delivered.
- Place the patient in the supine position.
- Inject ZIMHI into the anterolateral aspect of the thigh (through clothing, if necessary). Instruct patients to the correct location for injection.
- Immediately after injection, using one hand with fingers behind the needle, slide the safety guard over the needle. Do not use two hands to activate the Safety guard. Put the used syringe into the blue case and close the case.
- Seekemergencymedical careimmediatelyfollowing administration of ZIMHI.
- Place the patient in the lateral recumbent position (recovery position) as shown in the Instructions for Use.
- Additional supportive and/or resuscitative measures may be helpful while awaiting emergency medical assistance.
- Administer additional doses of ZIMHI every two to three minutes if the patient does not respond or relapses back into respiratory depression before emergency assistance arrives.
- If an accidental needlestick occurs seek medical attention immediately. Potential exposure to blood borne pathogens including HIV, HBV, and HCV requires immediate evaluation by a medical professional at an emergency room, urgent care, or your primary care provider. In addition, report accidental needle injury or device malfunction to ZMI Pharma Pharmacovigilance at (800) 230-3935.
- Complete patient information, including dosage, directions for proper administration, and precautions can be found inside each ZIMHI case or carton. A printed label on the surface of the ZIMHI case or carton shows instructions for use.
- During storage, periodically visually inspect the naloxone solution through the viewing window. If the solution is discolored yellow or brown color, cloudy or contains particles, replace ZIMHI with a new one.
- Replace ZIMHI before its expiration date.

Manufactured for ZMI Pharma, Carlsbad,, CA 92008, USA.

Distributed By FFF Enterprises Corp., 44000 Winchester Road, Temecula, CA 92590.

PATIENT PACKAGE INSERT

This Patient Information has been approved by the U.S. Food and Drug Administration.

PATIENT INFORMATION

ZIMHI® (ZIM-hye)
(naloxone hydrochloride injection, USP)
Prefilled syringe
for Intramuscular or Subcutaneous Use

You and your caregivers should read this Patient Information leaflet before an opioid emergency happens. This information does not take the place of talking with your healthcare provider about your medical condition or your treatment.

What is the most important information I should know about ZIMHI?ZIMHI is used to temporarily reverse the effects of opioid medicines. The medicine in ZIMHI has no effect in people who are not taking opioid medicines. Always carry ZIMHI with you in case of an opioid emergency.

- Use ZIMHI right away if you or your caregiver think signs or symptoms of an opioid emergency are present, even if you are not sure, because an opioid emergency can cause severe injury or death. Signs and symptoms of an opioid emergency may include:
  - unusual sleepiness and you are not able to awaken the person with a loud voice or rubbing firmly on the middle of their chest (sternum)
  - breathing problems including slow or shallow breathing in someone difficult to awaken or they look like they are not breathing
  - the black circle in the center of the colored part of the eye (pupil) is very small, sometimes called “pinpoint pupils” in someone difficult to awaken
- Family members, caregivers, or other people who may have to use ZIMHI in an opioid emergency should know where ZIMHI is stored and how to give ZIMHI before an opioid emergency happens. Make sure everyone reads the information contained in the case and carton as soon as you receive ZIMHI.
- ZIMHI is intended to be given by people 12 years of age or older. Younger children or those with limited hand strength may find the Pre-filled syringe difficult to use.
- Get emergency medical help right away after using the first dose of ZIMHI. Rescue breathing or CPR (cardiopulmonary resuscitation) may be given while waiting for emergency medical help.
- The signs and symptoms of an opioid emergency can return after ZIMHI is given. If this happens, give additional injections using a new ZIMHI pre-filled syringe every 2 to 3 minutes and watch the person closely until emergency help is received.
- ZIMHI is a prescription medicine used in adults and children for the treatment of an opioid emergency such as an overdose or a possible opioid overdose with signs of breathing problems and severe sleepiness or not being able to respond.
- ZIMHI is to be given right away by a caregiver and does not take the place of emergency medical care. Get emergency medical help right away after the first dose of ZIMHI, even if the person wakes up.
- ZIMHI is safe and effective in children for known or suspected opioid overdose.
- have heart problems
- are pregnant or plan to become pregnant. Use of ZIMHI may cause withdrawal symptoms in your unborn baby. Your unborn baby should be examined by a healthcare provider right away after you use ZIMHI.
- are breastfeeding or plan to breastfeed. It is not known if ZIMHI passes into your breast milk.

What is ZIMHI?

Who should not use ZIMHI?

Do not use ZIMHI if you are allergic to naloxone hydrochloride or any of the ingredients in ZIMHI. See the end of this leaflet for a complete list of ingredients in ZIMHI.

What should I tell my healthcare provider before using ZIMHI?

Before using ZIMHI, tell your healthcare provider about all of your medical conditions, including if you:

Tell your healthcare provider about the medicines you take, including prescription and over-the-counter medicines, vitamins, and herbal supplements.

How should I use ZIMHI?

Read the “Instructions for Use” at the end of this Patient Information leaflet for detailed information about the right way to use ZIMHI.

- Use ZIMHI exactly as prescribed by your healthcare provider.
- Each ZIMHI Pre-filled syringe contains only 1 dose of medicine and cannot be reused.
- ZIMHI should be injected into the muscle (intramuscular) or underneath the skin (subcutaneous) of the outer thigh. It can be injected through your clothing if needed.
- Caregivers should pinch the thigh muscle while injecting ZIMHI into a child under the age of 1 year old.
- When removing the needle cap there may be a drop of liquid on the needle: this is normal. The device contains an excess of liquid to ensure the required dose is delivered.
- If an accidental needlestick injury occurs, get emergencymedical help right away.Accidental needlestick injuries may put you at risk for blood borne diseases (such as HIV, HBV, and HCV) that can cause illness or death. In addition, report an accidental needlestick injury or problems with the ZIMHI Pre-filled syringe to ZMI Pharma Pharmacovigilance at (800) 230-3935.

What are the possible side effects of ZIMHI?

ZIMHI may cause serious side effects, including:

- Sudden opioid withdrawal symptoms. In someone who has been using opioids regularly, opioid withdrawal symptoms can happen suddenly after receiving ZIMHI and may include:

○ body aches

○ fever

○ sweating

○ runny nose

○ sneezing

○ goose bumps

○ yawning

○ weakness

○ shivering or trembling

○ nervousness

○ restlessness or irritability

○ diarrhea

○ nausea or vomiting

○ stomach cramping

○ increased blood pressure

○ increased heart rate

The most common side effects of ZIMHI include: nausea, dizziness, lightheadedness, and increased amounts of red blood cell breakdown products (bilirubin) in your blood.

In infants under 4 weeks old who have been receiving opioids regularly, sudden opioid withdrawal may be life-threatening if not treated the right way. Signs and symptoms include: seizures, crying more than usual and increased reflexes.

These are not all of the possible side effects of ZIMHI. Call your doctor for medical advice about side effects. You may report side effects to FDA at 1-800-FDA-1088.

How should I store ZIMHI?

- Store below 77°F (25°C).
- Excursions permitted up to 104°F (40°C).
- Do Not Freeze or expose to excessive heat above 104°F (40°C). Protect from Light.
- During storage, check ZIMHI often through the viewing window of the pre-filled syringe. The solution should be clear. If the ZIMHI solution is discolored, cloudy, or contains solid particles, replace it with a new ZIMHI.
- Your ZIMHI has an expiration date. Replace it before the expiration date.

Keep ZIMHIand all medicines out of the reach of children.

General information about the safe and effective use of ZIMHI.

Medicines are sometimes prescribed for purposes other than those listed in a Patient Information leaflet. Do not use ZIMHI for a condition for which it was not prescribed. You can ask your pharmacist or healthcare provider for information about ZIMHI that is written for health professionals.

What are the ingredients in ZIMHI?

Active ingredient:naloxone hydrochloride

Inactive ingredients: sodium chloride, hydrochloric acid to adjust pH, and water for injection.

ZIMHI is not made with natural rubber latex.

INSTRUCTIONS FOR USE

Instructions for Use
ZIMHI® (ZIM-hye)
(naloxone hydrochloride injection)
Pre -filled syringe

Use ZIMHI for known or suspected opioid overdose in adults and children.

ZIMHI is intended to be administered by people 12 years of age or older.Younger children or those with limited hand strength may find the device difficult to use.

Read this Instructions for Use carefully before you use this product.

Before you need to use your ZIMHI syringe make sure your healthcare provider shows you the right way to use it. Parents, caregivers, and others who may be in a position to administer ZIMHI should also understand how to use it. If you have questions, ask your healthcare provider.

Get Ready to Use ZIMHI

ZIMHI works like a standard prefilled syringe.

ZIMHI is injected downwards, into the middle of the outer thigh, (as shown), through clothing if needed.

Ready to Use ZIMHI

Place the patient on their back.

When ready to inject, pull off cap to expose needle.

DO NOT put finger on top of the device.

In children under the age of 1 year old, pinch the thigh muscle while administering the dose.

Hold ZIMHI by finger grips only and slowly insert the needle into the thigh.

After needle is in thigh: Push the plunger all the way down until it clicks and hold for 2 seconds.

After Use

Right after the injection, using one hand with fingers behind the needle, slide the safety guard over the needle. Do not use two hands to activate the safety guard. Put the used syringe into the blue case and close the case.

Get Help

Get emergency medical help now

Tell healthcare provider that you gave an injection of naloxone hydrochloride.

Turn the patient on their side (recovery position) after giving ZIMHI.

Use second syringe if necessary

You may need a second ZIMHI syringe if symptoms continue or recur.

If symptoms return after an injection with ZIMHI, an additional injection using another ZIMHI pre-filled syringe may be needed. Give additional injections using a new ZIMHI pre-filled syringe every 2 to 3 minutes and continue to closely watch the person until emergency help is received. Using ZIMHI does not take the place of emergency medical care.

After use and Disposal

- ZIMHI is a single-dose pre-filled syringe that delivers a fixed dose of naloxone hydrochloride. The pre-filled syringe cannot be reused. It is normal for most of the medicine to remain in the syringe after the dose has been injected.
- The correct dose has been injected if the plunger has been pushed all the way down and the solution window is at least partially blocked.
- Tell the healthcare provider that you have received or administered an injection of naloxone hydrochloride. Show the healthcare provider where the injection was administered.
- Give your used ZIMHI syringe, contained in the blue case, to the healthcare provider for inspection and proper disposal.

For more information see Patient Information sheet or ask your healthcare provider.

How to Store —Keep ZIMHI in its plastic case nearby and ready for use at all times.

- Store below 77°F (25°C). Excursions permitted up to 104°F (40°C). Do Not Freeze or expose to excessive heat above 104°F (40°C).
- Store the ZIMHI syringe in its closed plastic case to protect from light.

Check Your Stored ZIMHI® Often - The solution should be clear when viewed through the window on the device. If the solution is discolored (yellowish or brown color), cloudy or contains particles, replace ZIMHI with a new one.

Your ZIMHI® Has an Expiration Date - Example YYYY-MM. Replace ZIMHI before the last day of expiration month. Dispose of expired ZIMHI properly by taking ZIMHI in its case to a healthcare provider or hospital emergency room.

For more information about ZIMHI pre-filled syringe and proper use of ZIMHI, call 1-800-230-3935 or visit www.ZIMHI.com.

ZIMHI is a registered trademark of ZMI Pharma Corporation.

Manufactured for ZMI Pharma, Carlsbad, CA 92008, USA.

Distributed By FFF Enterprises Corp. 44000 Winchester Road, Temecula, CA 92590..

This Instructions for Use has been approved by the U.S. Food and Drug Administration.

Revised: 08/2024

PRINCIPAL DISPLAY PANEL

NDC 84571- 140-02
Rx Only
ZIMHI
(naloxone HCL Injection, USP)
5 mg/ 0.5 mL